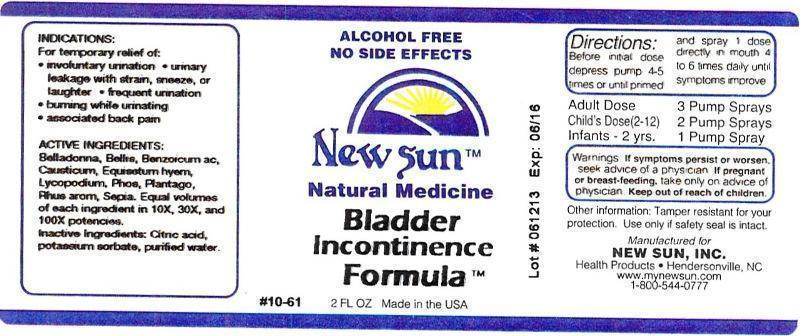 DRUG LABEL: Bladder Incontinence Formula
NDC: 66579-0078 | Form: LIQUID
Manufacturer: New Sun Inc.
Category: homeopathic | Type: HUMAN OTC DRUG LABEL
Date: 20140905

ACTIVE INGREDIENTS: ATROPA BELLADONNA 10 [hp_X]/59 mL; BELLIS PERENNIS 10 [hp_X]/59 mL; BENZOIC ACID 10 [hp_X]/59 mL; CAUSTICUM 10 [hp_X]/59 mL; EQUISETUM HYEMALE 10 [hp_X]/59 mL; LYCOPODIUM CLAVATUM SPORE 10 [hp_X]/59 mL; PHOSPHORUS 10 [hp_X]/59 mL; PLANTAGO MAJOR 10 [hp_X]/59 mL; RHUS AROMATICA ROOT BARK 10 [hp_X]/59 mL; SEPIA OFFICINALIS JUICE 10 [hp_X]/59 mL
INACTIVE INGREDIENTS: CITRIC ACID MONOHYDRATE; POTASSIUM SORBATE; WATER

Bladder Incontinence Formula

DOSAGE AND ADMINISTRATION

Directions: Before initial dose depress pump 4-5 times or until primed and spray 1 dose directly in mouth 4 to 6 times daily until symptoms improve.

Adult Dose: 3 Pump Sprays

Child's Dose (2-12): 2 Pump Sprays

Infants - 2 yrs: 1 Pump Spray

WARNINGS

Warnings: If symptoms persist or worsen, seek advice of a physician. If pregnant or breast-feeding, take only on advice of physician.

Keep out of reach of children.

Other information: Tamper resistant for your protection. Use only if safety seal is intact.

PURPOSE

Indications: For temporary relief of: •involuntary urination •urinary leakage with strain, sneeze, or laughter •frequent urination •burning while urinating •associated back pain

ACTIVE INGREDIENT

Active Ingredients: Belladonna, Bellis perennis, Benzoicum acidum, Causticum, Equisetum hyemale, Lycopodium clavatum, Phosphorus, Plantago major, Rhus aromatica, Sepia. Equal volumes of each ingredient in 10X, 30X, 100X potencies.

Inactive Ingredient: Citric acid, potassium sorbate, purified water.

Indications: For temporary relief of:

- involuntary urination
- urinary leakage with strain, sneeze, or laughter
- frequent urination
- burning while urinating
- associated back pain